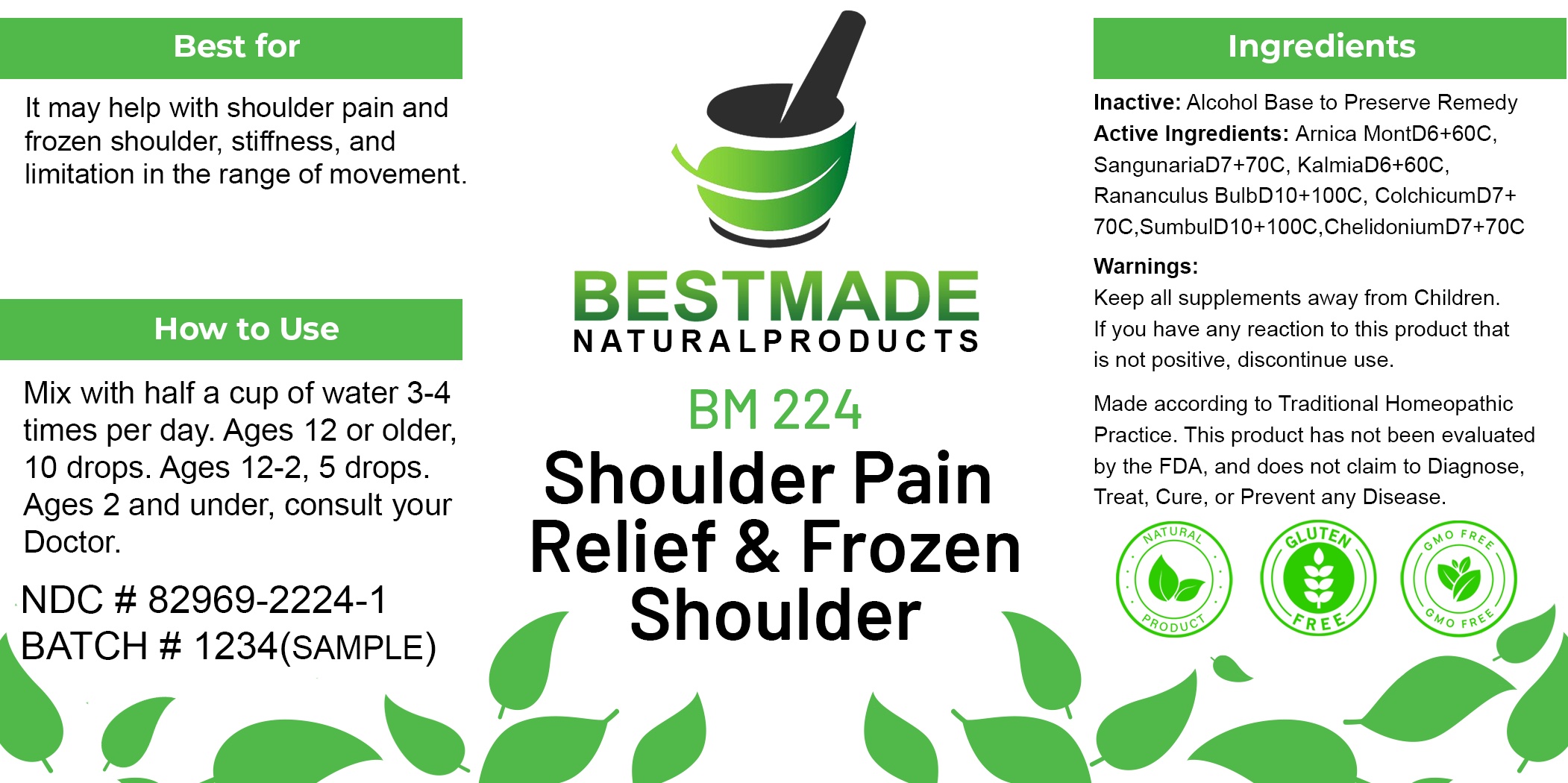 DRUG LABEL: Bestmade Natural Products BM224
NDC: 82969-2224 | Form: LIQUID
Manufacturer: Bestmade Natural Products
Category: homeopathic | Type: HUMAN OTC DRUG LABEL
Date: 20241218

ACTIVE INGREDIENTS: COLCHICUM AUTUMNALE FLOWER 30 [hp_C]/30 [hp_C]; CHELIDONIUM MAJUS WHOLE 30 [hp_C]/30 [hp_C]; SANGUINARIA CANADENSIS ROOT 30 [hp_C]/30 [hp_C]; RANUNCULUS BULBOSUS ROOT 30 [hp_C]/30 [hp_C]; KALMIA ANGUSTIFOLIA LEAF 30 [hp_C]/30 [hp_C]; ARNICA MONTANA 30 [hp_C]/30 [hp_C]; FERULA SUMBUL ROOT 30 [hp_C]/30 [hp_C]
INACTIVE INGREDIENTS: ALCOHOL 30 [hp_C]/30 [hp_C]

Shoulder Pain Support and Frozen Shoulder (BM224)

DOSAGE AND ADMINISTRATION

Mix with half a cup of water 3-4
times per day. Ages 12 or older,
10 drops. Ages 12-2, 5 drops.
Ages 2 and under, consult your
Doctor.

INDICATIONS AND USAGE

It may help with shoulder pain and
frozen shoulder. stiffness, and
limitation in the range of movement.

Inactive: Alcohol Base to Preserve Remedy

Active Ingredients: Arnica MontD6+60C,
SangunariaD7+70C, KalmiaD6+60C,
Rananculus BulbD10+100C, ColchicumD7+
70C.SumbulD10+100C ChelidoniumD7+70C

Keep all supplements away from children.
If you have any reaction to this product that is not positive, discontinue use.

Made according to Traditional Homeopathic Practice. This product has not been evaluated by the FDA, and does not claim to diagnose, treat, cure, or prevent any disease.

PURPOSE

It may help with shoulder pain and
frozen shoulder. stiffness, and
limitation in the range of movement.

WARNINGS

Keep all supplements away from children.
If you have any reaction to this product that is not positive, discontinue use.

Made according to Traditional Homeopathic Practice. This product has not been evaluated by the FDA, and does not claim to diagnose, treat, cure, or prevent any disease.

Entire package label.